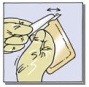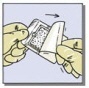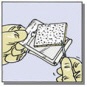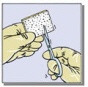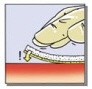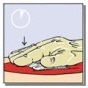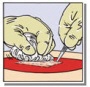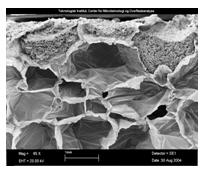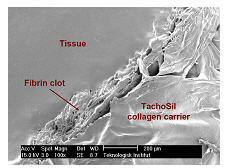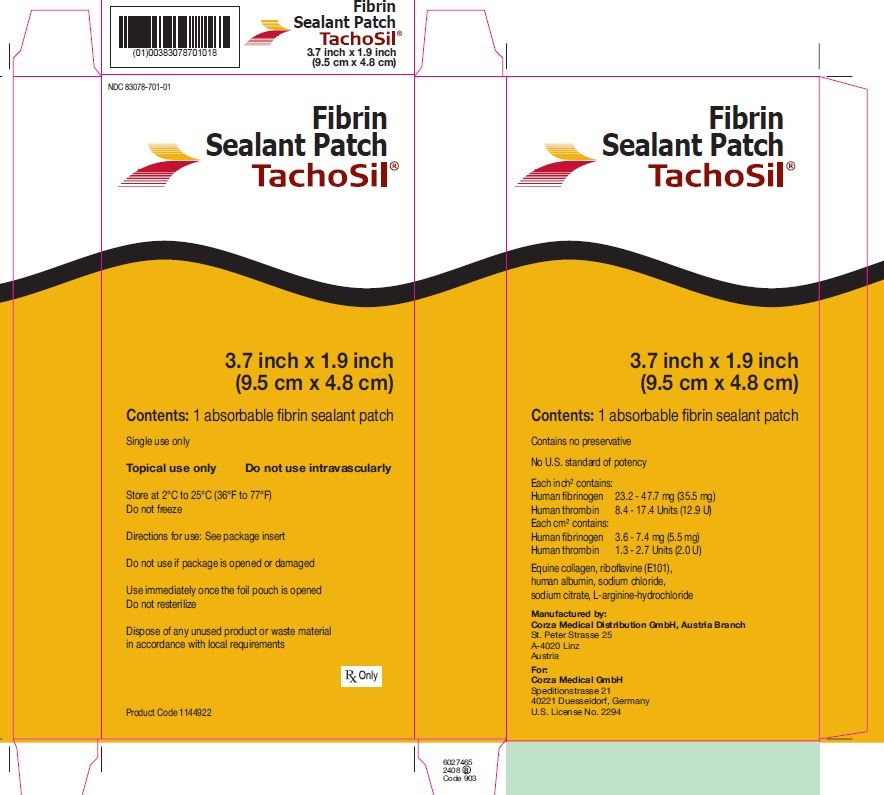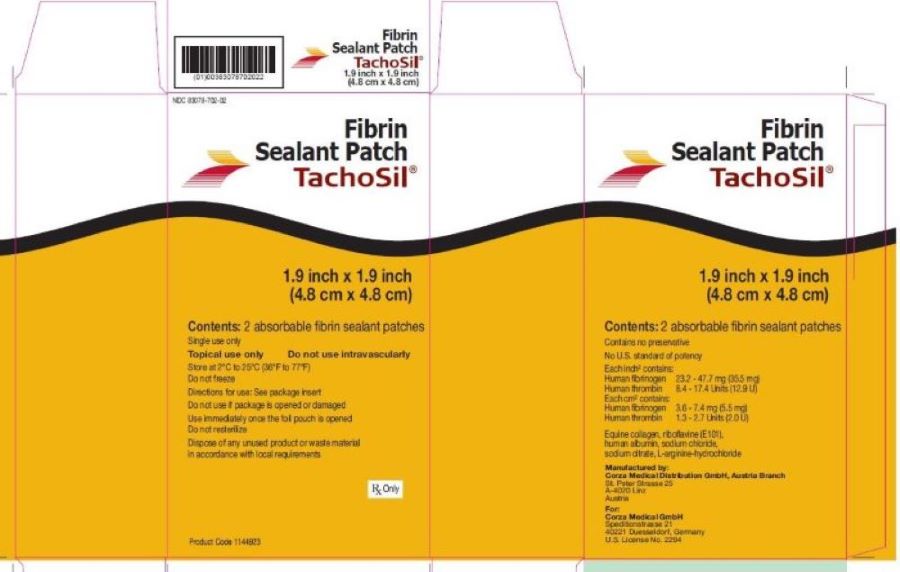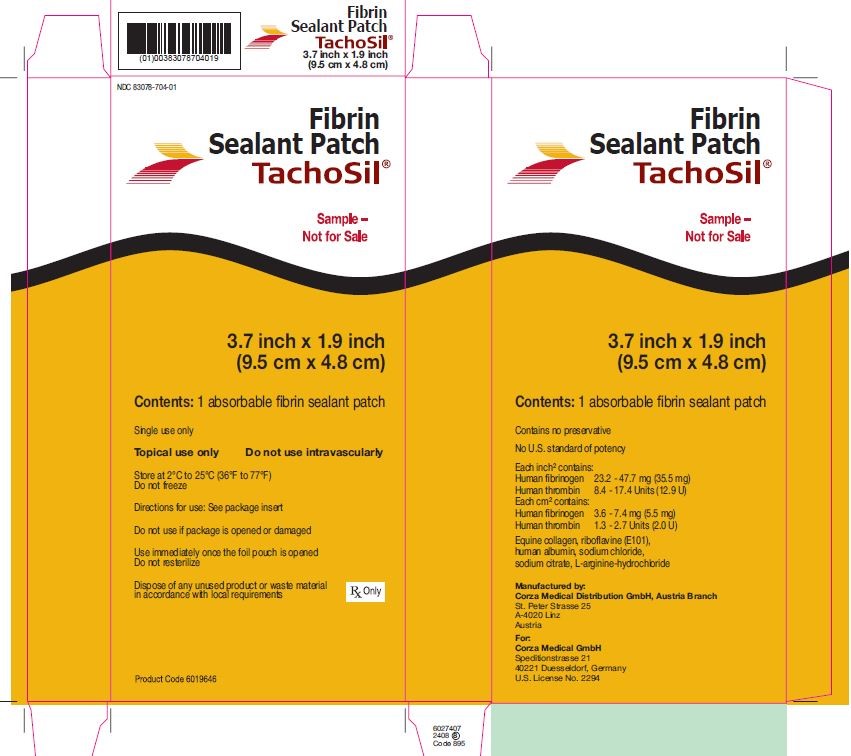 DRUG LABEL: TachoSil
NDC: 83078-701 | Form: PATCH
Manufacturer: Corza Medical GmbH
Category: prescription | Type: HUMAN PRESCRIPTION DRUG LABEL
Date: 20251008

ACTIVE INGREDIENTS: HUMAN THROMBIN 2.0 [USP'U]/1 1; FIBRINOGEN HUMAN 5.5 mg/1 1
INACTIVE INGREDIENTS: EQUINE COLLAGEN; ALBUMIN HUMAN; RIBOFLAVIN; SODIUM CHLORIDE; SODIUM CITRATE, UNSPECIFIED FORM; ARGININE HYDROCHLORIDE

HIGHLIGHTS OF PRESCRIBING INFORMATION

These highlights do not include all the information needed to use TACHOSIL safely and effectively. See full prescribing information for TACHOSIL.
TACHOSIL® Fibrin Sealant Patch
Absorbable Patch for Topical Use
Initial U.S. Approval: 2010

RECENT MAJOR CHANGES

Dosage and Administration (2.2) 08/2025

Warning and Precautions (5.6) 08/2025

1 INDICATIONS AND USAGE

TachoSil is a fibrin sealant patch indicated for use with manual compression in adult and pediatric patients as an adjunct to hemostasis in cardiovascular and hepatic surgery, when control of bleeding by standard surgical techniques (such as suture, ligature or cautery) is ineffective or impractical. (1)

Limitations for Use

Not for use in place of sutures or other forms of mechanical ligation in treatment of major arterial or venous bleeding. (1)

Not for use in children under one month of age. (8.4)

2 DOSAGE AND ADMINISTRATION

Apply on the surface of cardiovascular or hepatic tissue only.

- Determine the number of TachoSil patches to be applied by the size of the bleeding area. (2)
- Apply the yellow, active side of the patch to the bleeding surface. (2)

3 DOSAGE FORMS AND STRENGTHS

- TachoSil is a topical fibrin sealant patch consisting of human fibrinogen and human thrombin coated onto an equine collagen sponge.
- Each absorbable patch contains, per square inch (inch^2): human fibrinogen 23.2 to 47.7 mg (35.5 mg); human thrombin 8.4 to 17.4 Units (12.9 U) per cm^2: human fibrinogen 3.6 to 7.4 mg (5.5 mg); human thrombin 1.3 to 2.7 Units (2.0 U). (3)

4 CONTRAINDICATIONS

- Do not apply TachoSil intravascularly. Intravascular application of TachoSil may result in life-threatening thromboembolic events. (4)
- Do not use TachoSil in individuals with known hypersensitivity to human blood products or horse proteins. (4)

5 WARNINGS AND PRECAUTIONS

- Thrombosis can occur if TachoSil is applied intravascularly. Ensure that TachoSil is applied to the surface of cardiac, vascular or hepatic tissue only. (5.1)
- Can cause hypersensitivity or allergic/anaphylactoid reactions with first time or repetitive application. (5.2)
- Avoid use in contaminated areas of the body or in the presence of an active infection. (5.3)
- TachoSil contains collagen, which may adhere to bleeding surfaces. May carry a risk of gastrointestinal obstruction in abdominal surgery due to tissue adhesions. To prevent the development of tissue adhesions at undesired sites, ensure tissue areas outside the application area are adequately cleansed before administration of TachoSil. (5.4)
- Avoid packing in cavities or closed spaces, because this may cause compression of underlying tissue. (5.5)
- Use the least number of patches required to cover the entire bleeding area. Do not pack. Remove any unattached pieces of TachoSil. (5.6)
- May carry a risk of transmitting infectious agents, such as viruses, and theoretically, the variant Creutzfeldt-Jakob disease (vCJD) agent, and the Creutzfeldt-Jakob disease (CJD) agents, despite manufacturing steps designed to reduce the risk of viral transmission. (5.7)

6 ADVERSE REACTIONS

The most common adverse reactions reported in >1% of patients during clinical trials were anemia, nausea and vomiting, fever, abdominal pain, increased white blood cell count, ascites, itching, atrial fibrillation, pleural effusion, gastrointestinal hemorrhage, wound infection, hypophosphatemia, urinary tract infection and post-procedural bile leakage in hepatic surgery. (6.1)

To report SUSPECTED ADVERSE REACTIONS, contact Corza Medical GmbH at 1-800-997-1067 or FDA at 1-800-FDA-1088 or www.fda.gov/medwatch.

FULL PRESCRIBING INFORMATION

1 INDICATIONS AND USAGE

TachoSil is a fibrin sealant patch indicated for use with manual compression in adult and pediatric patients as an adjunct to hemostasis in cardiovascular and hepatic surgery when control of bleeding by standard surgical techniques (such as suture, ligature or cautery) is ineffective or impractical.

Limitations for Use

- TachoSil cannot safely or effectively be used in place of sutures or other form of mechanical ligation for the treatment of major arterial or venous bleeding.
- Not for use in children under one month of age.

2 DOSAGE AND ADMINISTRATION

For topical use on cardiovascular or hepatic tissue only

- Determine the number of patches to be applied by the size of the bleeding area.
- Apply the yellow, active side of the patch to the bleeding area.
- When applying TachoSil, do not exceed the maximum number of patches shown in Table 1 [see Warnings and Precautions (5.6)].

Table 1. Amount of Fibrinogen and Thrombin per Total Patch Size
and Maximum Number of TachoSil Patches to be Applied
TachoSil Patch Size | Human Fibrinogen (mg) | Human Thrombin (Units) | Maximum Number of Patches to be Applied
3.7 inch x 1.9 inch (9.5 cm x 4.8 cm) | 337.4 | 123.1 | 10
1.9 inch x 1.9 inch (4.8 cm x 4.8 cm) | 170.5 | 62.2 | 14

2.1 Preparation for Application

TachoSil comes ready to use in sterile packages and must be handled using sterile technique in aseptic conditions. Discard damaged packages as resterilization is not possible.

- When in the operating room, the outer aluminum foil pouch may be opened in a non-sterile environment (Fig. 1A). The inner sterile blister must be opened in a sterile environment (Fig. 1B).
- Remove the TachoSil patch from the blister (Fig. 1C), which can be used as a container for pre-moistening of the patch, if needed.
- Determine the size of patch(es) to be applied to the bleeding surface. Select the appropriate TachoSil patch so that it extends 1 to 2 cm beyond the margins of the wound. The patch can be cut to the correct size and shape if desired (Fig. 1D). If more than one patch is used, overlap patches by at least 1 cm.
- Prior to application, cleanse the area to be treated to remove disinfectants and other fluids. The fibrinogen and thrombin proteins can be denatured by alcohol, iodine or heavy metal ions. If any of these substances have been used to clean the wound area, thoroughly irrigate the area before the application of TachoSil.
- Apply TachoSil directly to the bleeding area either wet or dry. If applied wet, pre-moisten TachoSil in 0.9% saline solution and then apply immediately. In the case of a wet tissue surface (e.g., oozing bleeding) TachoSil may be applied without pre-moistening.

Figure 1: Pictures illustrating steps for preparation for application of TachoSil

A

B

C

D

2.2 Method of Application

To ensure TachoSil adheres effectively, follow the recommended handling, preparation, and application procedures. Incorrect handling may result in non-adherence and reduced efficacy of TachoSil.

- Cleanse surgical instruments, gloves and adjacent tissues with saline solution to reduce the adherence to the TachoSil patch. The white, inactive side of TachoSil may also adhere to surgical instruments (e.g., forceps), gloves or adjacent tissues covered with blood due to the affinity of collagen to blood. It is important to note that failure to adequately clean adjacent tissues may cause adhesions [see Warnings and Precautions (5.4)].
- Apply the yellow, active side of the patch to the bleeding area (Fig. 2A) and hold in place with gentle pressure applied through moistened gloves or a moist pad for at least three minutes (Fig. 2B).
- To avoid pulling the patch loose, first place a clean surgical instrument at one end of the patch before relieving the pressure (Fig. 2C). Gentle irrigation may also aid in removing the pre-moistened pad or gloved hand without removing TachoSil from the bleeding area.
- Leave TachoSil in place once it adheres to organ tissue. Only remove unattached TachoSil patches (or part of) and replace with new patches.
- TachoSil cannot be resterilized once removed from inner pouch. Discard unused, opened packages of TachoSil at the end of the procedure.

Figure 2: Pictures illustrating steps for method of application of TachoSil

A

B

C

Record patient name and TachoSil batch number every time that TachoSil is administered to a patient.

2.3 Retreatment

If not satisfied with the placement of the patch, or if bleeding still occurs during or after the specified duration of compression, repeat application procedure above. Do not remove already applied TachoSil.

3 DOSAGE FORMS AND STRENGTHS

TachoSil is a topical fibrin sealant patch consisting of human fibrinogen and human thrombin coated onto an equine collagen sponge. The active side of the patch is yellow in color due to the presence of a colorant riboflavin (E101); and the non-active side is off-white in color.

Strength:

Each absorbable TachoSil patch contains:

Per square inch:

Human fibrinogen 23.2 – 47.7 mg (35.5 mg)

Human thrombin 8.4 – 17.4 Units (12.9 U)

Per square centimeter:

Human fibrinogen 3.6 – 7.4 mg (5.5 mg)

Human thrombin 1.3 – 2.7 Units (2.0 U)

4 CONTRAINDICATIONS

Do not use TachoSil for:

- Intravascular application. Bleeding from large defects in visible arteries or veins where the injured vascular wall requires repair and maintenance of vessel patency or where there would be persistent exposure of TachoSil to blood flow during absorption of the product. This can result in life-threatening thromboembolic events [see Warnings and Precautions (5.1)].
- Individuals known to have anaphylactic or severe systemic reaction to human blood products or horse proteins [see Warnings and Precautions (5.2)].

5 WARNINGS AND PRECAUTIONS

5.1 Thrombosis

Thrombosis can occur if TachoSil is applied intravascularly. Ensure that TachoSil is applied to the surface of cardiac, vascular, or hepatic tissue only.

5.2 Hypersensitivity Reactions

Hypersensitivity or allergic/anaphylactoid reactions may occur with TachoSil. Symptoms associated with allergic anaphylactic reactions include: flush, urticaria, pruritus, nausea, drop in blood pressure, tachycardia or bradycardia, dyspnea, severe hypotension and anaphylactic shock. These reactions may occur in patients receiving TachoSil for the first time or may increase with repetitive applications of TachoSil.

5.3 Infection

Avoid application to contaminated or infected areas of the body, or in the presence of active infection.

5.4 Adhesions

TachoSil contains collagen, which may adhere to bleeding surfaces.

To prevent the development of tissue adhesions at undesired sites, ensure tissue areas outside the desired application area are adequately cleansed before administration of TachoSil [see Dosage and Administration (2.2)]. Events of adhesions to gastrointestinal tissues leading to gastrointestinal obstruction have been reported with use in abdominal surgery carried out in proximity to the bowel.

5.5 Compression

When placing TachoSil into cavities or closed spaces, avoid packing because this may cause compression of underlying tissue.

5.6 Non-Adherence or Dislodged Material

Non-adherence has occurred after TachoSil application [see Postmarketing Experience (6.2)]. Follow proper handling, preparation, and application procedures to reduce the risk of non-adherence of TachoSil [see Dosage and Administration (2.2)].

Theoretically, excess patch material can become dislodged and migrate to other areas of the body. Use only minimum amount of TachoSil patches necessary to achieve hemostasis. Remove unattached pieces of TachoSil; if medically necessary [see Dosage and Administration (2.2)].

5.7 Transmissible Infectious Agents

Because the biological components of this product are made from human blood, it may carry a risk of transmitting infectious agents (e.g., viruses), and theoretically, the variant Creutzfeldt-Jakob disease (vCJD) agent and the Creutzfeldt-Jakob disease (CJD) agent. The risk that TachoSil will transmit an infectious agent has been reduced by screening plasma donors for prior exposure to certain viruses, by testing for the presence of certain virus infections, and by inactivating and removing, certain viruses [see Description (11)]. Despite these measures, such products can still potentially transmit disease. There is also the possibility that unknown infectious agents may be present in such products.

All infections thought by a physician possibly to have been transmitted by this product should be reported by the physician or other healthcare provider to Corza Medical GmbH, at telephone number 1-800-997-1067. The physician should discuss the risks and benefits of this product with the patient.

Some viruses, such as parvovirus B19, are particularly difficult to remove or inactivate at this time. Parvovirus B19 most seriously affects pregnant women (fetal infection); immune-compromised individuals or individuals with an increased erythropoiesis (e.g., hemolytic anemia) [see Use in Specific Populations (8.1) and Patient Counseling Information (17)].

6 ADVERSE REACTIONS

The adverse reactions reported in more than one percent of patients during clinical trials were anemia, nausea and vomiting, fever, abdominal pain, increased white blood cell count, ascites, itching, atrial fibrillation, pleural effusion, gastrointestinal hemorrhage, wound infection, hypophosphatemia, urinary tract infection, and post-procedural bile leakage in hepatic surgery.

6.1 Clinical Trials Experience

Because clinical trials are conducted under widely varying conditions, adverse reaction rates observed in the clinical trials of a drug cannot be directly compared to rates in the clinical trials of another drug and may not reflect the rates observed in practice.

Cardiovascular Surgery

In the cardiovascular trial, the most frequently reported adverse reactions were atrial fibrillation and pleural effusion. Seventy-four percent (74%) of patients treated with TachoSil and 75% of comparator treated patients experienced one or more clinically relevant adverse reactions (see Table 2).

Table 2. Most Frequent Adverse Reactions (Cardiovascular Trial)
Adverse Reaction | TachoSil | Comparator [Comparator: Hemostatic fleece material without additional active coagulation stimulating compounds.]
Adverse Reaction | N = 62 [As treated population (safety data set).] n (%) | N = 57 n (%)
Atrial fibrillation | 18 (29%) | 14 (25%)
Pleural effusion | 14 (23%) | 11 (19%)
Pyrexia | 4 (6%) | 3 (5%)

Hepatic Surgery

In the hepatic surgery trial, the most frequently reported adverse reactions were nausea and anemia (see Table 3). Ninety-four percent (94%) of patients treated with TachoSil and 94% of comparator treated patients experienced one or more clinically relevant adverse reactions.

Table 3. Most Frequent Adverse Reactions (Hepatic Resection Trial)
Adverse Reaction | TachoSil | Comparator [Comparator: Hemostatic fleece material without additional active coagulation stimulating compounds.]
Adverse Reaction | N = 114 [As treated population (safety data set).] n (%) | N = 109 n (%)
Nausea | 34 (30%) | 29 (27%)
Anemia | 26 (23%) | 23 (21%)

Post-operative bile leakage was observed in 8 (7%) of patients after treatment with TachoSil and 13 (12%) after treatment with comparator.

Immunogenicity

Antibodies against components of fibrin sealant/hemostatic products may occur.

However in a clinical trial with human fibrinogen/human thrombin sponge (patch) in hepatic surgery, in which patients were investigated for the development of antibodies, 26% of the 96 patients tested and treated with human fibrinogen/human thrombin sponge (patch) developed antibodies to equine collagen. The equine collagen antibodies that developed in some patients after human fibrinogen/human thrombin sponge (patch) use were not reactive with human collagen. One patient developed antibodies to human fibrinogen.

There were no adverse events attributable to the development of human fibrinogen or equine collagen antibodies.

There is very limited clinical data available regarding re-exposure of the human fibrinogen/human thrombin sponge (patch). Two subjects have been re-exposed in a clinical trial and have not reported any immune-mediated adverse events, however, their antibody status to collagen or fibrinogen is unknown.

Pediatric Clinical Trial Experience

In pediatric patients, the most frequently reported adverse reactions were diarrhea, hypertension and increased transaminases (see Table 4). Ninety-four percent (94%) of patients treated with TachoSil and 100% of comparator treated patients experienced one or more clinically relevant adverse reactions.

Table 4. Most Frequent Adverse Reactions in Pediatric Patients (All Trials)
Adverse Reaction | TachoSil | Comparator [Comparator: Hemostatic fleece material compounds without additional active coagulation stimulating compounds.]
Adverse Reaction | N = 36 [As treated population (safety data set).] n (%) | N = 9 n (%)
Diarrhea | 6 (17%) | 0
Hypertension | 6 (17%) | 1 (11%)
Transaminases Increased | 4 (11%) | 0

6.2 Postmarketing Experience

The following adverse reactions have been identified during post-approval use of TachoSil. Because these reactions are reported voluntarily from a population of uncertain size, it is not always possible to reliably estimate their frequency or establish a causal relationship to drug exposure.

The following adverse reactions have been reported in postmarketing experience with TachoSil:

General disorders and administration site conditions: adhesions, drug ineffective or non-adherence of TachoSil, inflammation, granuloma, catheter-related complication, multi-organ failure

Injury, poisoning and procedural complications: foreign body trauma, post-procedural pulmonary embolism

Vascular disorders: thrombosis

Infections and infestations: hepatitis C

Respiratory, thoracic and mediastinal disorders: respiratory distress, laryngeal edema, hemothorax

Blood and lymphatic system disorders: splenic hemorrhage, eosinophilia

Renal and urinary disorders: renal artery thrombosis, renal failure

Endocrine disorders: parathyroid disorder

Eye disorders: mydriasis

Nervous system disorders: nerve compression

Gastrointestinal disorders: intestinal obstruction (in abdominal surgeries), ileus (in abdominal surgeries)

8 USE IN SPECIFIC POPULATIONS

8.1 Pregnancy

TERATOGENIC EFFECTS

Risk Summary

A review of available data suggests that major birth defects occur in 2-4% of the U.S. general population and that miscarriage occurs in 15-20% of clinically recognized pregnancies, regardless of drug exposure. Animal reproduction studies have not been conducted with TachoSil. There are no adequate and well-controlled studies in pregnant women. It is also not known whether TachoSil can cause fetal harm when administered to a pregnant woman or can affect reproduction capacity. TachoSil should be administered to pregnant women only if clearly needed.

8.2 Lactation

It is not known whether this drug is excreted in human milk. Because many drugs are excreted in human milk, caution should be exercised when TachoSil is administered to nursing mothers.

8.4 Pediatric Use

The use of TachoSil has been studied in patients aged one month to 16 years; use in children under the age of one month may be unsafe or ineffective due to small size and limited ability to apply the patch as recommended. Use of TachoSil in the one month to 16 years age group is supported by evidence from adequate and well-controlled studies of TachoSil in adults with additional data from two clinical trials, which included 36 pediatric patients at the age of 16 years or younger. The data supports the use of TachoSil for hemostasis in pediatric patients undergoing cardiovascular and hepatic surgery [see Clinical Studies (14.3)].

8.5 Geriatric Use

Clinical trials to date included 326 patients older than 65 years of age receiving TachoSil. No overall differences in safety or effectiveness were observed between the elderly and younger patients, however, greater susceptibility of some older patients to adverse reactions cannot be ruled out.

11 DESCRIPTION

TachoSil Fibrin Sealant Patch is a sterile, bioabsorbable combination product comprised of two active substances (human plasma-derived fibrinogen and human plasma-derived thrombin) coated onto a collagen sponge of equine origin. The collagen sponge serves as a flexible and mechanically stable carrier for the active substances to facilitate application of the human fibrinogen and thrombin to the wound surface. The active side of the patch is yellow in color due to the presence of a colorant riboflavin (E101); and the non-active side is off-white in color. Each square inch of the patch contains approximately 35.5 mg of human fibrinogen and 12.9 units of human thrombin. Other inactive ingredients include equine collagen, human albumin, sodium chloride, sodium citrate, and L‑arginine hydrochloride.

TachoSil is sterilized by gamma irradiation after completion of inner and outer packaging, resulting in a sterile product in a sterile inner package.

Viral Clearance

The active biological substances of TachoSil (human fibrinogen and human thrombin) are manufactured from pooled human plasma collected in facilities in the United States. Human plasma is tested by a Nucleic Acid Test (NAT) for hepatitis B virus (HBV), hepatitis C virus (HCV), and human immunodeficiency virus-1 (HIV-1). NAT testing for hepatitis A virus (HAV) and parvovirus B19 is also performed. Human plasma is also tested for the presence of hepatitis B surface antigen (HBsAg), and antibodies to hepatitis C virus (anti-HCV) and human immunodeficiency viruses types 1 and 2 (anti-HIV 1/2).

The manufacturing procedure for each TachoSil component and final product include processing steps designed to reduce the risk of viral transmission. In particular, the virus clearance steps in the manufacture of human fibrinogen and thrombin include pasteurization, precipitation and adsorption. The virus clearance step in the manufacture of the collagen sponge is the pH treatment.

The virus clearance capacity of these procedures in the manufacture of fibrinogen, thrombin and collagen sponge has been validated using viruses with a wide range of physicochemical characteristics. These in vitro validation studies were conducted using samples from manufacturing intermediates spiked with virus suspensions of known titers followed by further processing under conditions equivalent to those in the respective manufacturing steps. The cumulative virus reduction factors (expressed as log10) are shown in Table 5 for each virus tested.

Table 5. Cumulative Virus Reduction Factors for the Components of TachoSil
Cumulative Reduction Factors for Virus Removal/Inactivation of Human Thrombin
 | Virus Reduction Factors [log10]
Manufacturing step | Enveloped Viruses |  |  |  | Non-enveloped Viruses
Manufacturing step | HIV [HIV: Human Immunodeficiency Virus,] | HSV [HSV: Herpes Simplex Virus] | BVDV [BVDV: Bovine Viral Diarrhea Virus] | PRV [PRV: Pseudorabies Virus] | CPV [CPV: Canine parvovirus] | HAV [HAV: Hepatitis A Virus]
Pasteurization, precipitation and adsorption steps | 15.0 | 20.4 | 13.2 | 16.3 | 5.4 | 8.4
Cumulative Reduction Factors for Virus Removal/Inactivation of Human Fibrinogen
 | Virus Reduction Factors [log10]
Manufacturing step | Enveloped Viruses |  |  |  | Non-enveloped Viruses
Manufacturing step | HIV | PRV | BVDV | WNV [WNV: West Nile Virus, only single manufacturing step validated] | CPV | HAV
Pasteurization, precipitation and lyophilization steps | 9.6 | 8.8 | 11.2 | 8.3 | 4.9 | 8.6
Reduction Factors for Virus Removal/Inactivation of the Collagen Sponge (equine)
 | Virus Reduction Factors [log10]
Manufacturing step | Enveloped Viruses |  |  |  | Non-enveloped Viruses
Manufacturing step | PRV |  | PI-3 [PI-3: Parainfluenza Virus type 3] |  | PPV [PPV: Porcine Parvovirus] | Reo3 [Reo 3: ReoVirus type 3]
pH treatment | 5.7 |  | 5.9 |  | --- | ---

A validation study was also conducted to evaluate the capacity for gamma irradiation to inactivate and/or remove viruses in the final TachoSil product. The virus reduction factors (expressed as log10) are shown in Table 6 for each virus tested.

Table 6. Virus Reduction Factors for TachoSil Final Sterilization by Gamma Irradiation
Reduction Factor of Gamma Irradiation (Final Sterilization of TachoSil)
 | Virus Reduction Factors [log10]
 | Enveloped Viruses |  | Non-enveloped Viruses
Manufacturing step | PRV [PRV: Pseudorabies Virus] | PI-3 [PI-3: Parainfluenza Virus type 3] | PPV [PPV: Porcine Parvovirus] | Reo3 [Reo 3: ReoVirus type 3]
Gamma Irradiation | 4.7 | 4.0 | 3.0 | 6.2

All infections considered by a physician possibly to have been transmitted by this product should be reported to Corza [see Warnings and Precautions (5.7)].

12 CLINICAL PHARMACOLOGY

12.1 Mechanism of Action

The mechanism of action of TachoSil is based on the interaction between the active biological substances (human fibrinogen and human thrombin) and the physiology of the fibrin clot formation (Fig. 3A). Upon contact with a bleeding wound surface, the active substances coated onto the equine collagen patch become dissolved and partly diffuse into the wound surface. The subsequent fibrinogen-thrombin reaction initiates the last step in the cascade of biochemical reactions-conversion of fibrinogen into fibrin monomers that further polymerize to form the fibrin clot.

Hemostasis is achieved when the formed fibrin clot adheres the collagen patch to the wound surface, thus providing a physical barrier to bleeding (Fig 3B). TachoSil exhibits flexibility to accommodate for the physiological movements of tissues and organs and can withstand pressures up to 61.4 hPa (46.1 mmHg).

Figure 3: Scanning Electron Microscopy Photos of TachoSil

A. The side view of the TachoSil patch shows the coating of the human plasma components anchored to the indentations of the collagen carrier.

B. The deposition of a fibrin clot formed from fibrinogen and thrombin of the coating results in hemostasis and conglutination of the TachoSil patch to the wound surface.

13 NONCLINICAL TOXICOLOGY

13.1 Carcinogenesis, Mutagenesis, Impairment of Fertility

Long-term animal studies to evaluate the carcinogenic potential of TachoSil or studies to determine the genotoxicity or the effect of TachoSil on fertility have not been performed. An assessment of the carcinogenic potential of TachoSil was completed to demonstrate minimal carcinogenic risk from product use.

13.2 Animal Toxicology and/or Pharmacology

In a study conducted in swine, TachoSil was applied to liver wounds and showed progressive degradation. However, remnants of the TachoSil patch may remain present for more than 12 months. Histologic examination at 26 and 52 weeks revealed that granulation tissue encapsulates TachoSil remnants and forms a firm capsule around them. Remnants were found in all treated animals after 26 weeks (12/12) and in most animals (6/8) after 52 weeks. No other local reactivity or toxicities were noted.

14 CLINICAL STUDIES

14.1 Cardiovascular

An open-label, multi-center, randomized, parallel-group study comparing TachoSil with comparator (hemostatic fleece without additional active coagulation stimulating compounds) treatment was conducted to evaluate TachoSil for control of bleeding in 119 patients undergoing cardiovascular surgery requiring cardiopulmonary bypass procedure. Of the 119 subjects, 88 (74%) were male and 31 (26%) female. Mean (range) age was 67 (23 to 86) years; subjects older than 65 years constituted 58% of the male and 74% of the female population. All subjects were White/Caucasian.

In the Intent-to-Treat (ITT) population, 59 patients were randomized to treatment with TachoSil and 60 patients were randomized to treatment with the comparator. A larger proportion of patients in the TachoSil treatment group (44/59; 75%) than in the comparator treatment group (20/60; 33%) achieved hemostasis within three minutes, which was a statistically significant difference (p<0.0001).

Fifty-six out of 59 (95%) patients in the TachoSil treatment group achieved hemostasis at six minutes compared to 43 out of 60 (72%) in the comparator treatment group, which also was statistically significant (p=0.0006) (see Table 7).

Table 7. Efficacy Results in Cardiovascular Surgery, by Treatment, Intent-to-Treat Population
Treatment | Total number of patients who achieved hemostasis | Percentage of patients who achieved hemostasis | 95% CI for proportion [Normal approximation to the binominal distribution is used to construct the asymptotic confidence intervals] | p-value [Cochran-Mantel-Haenszel test controlling for center]
Hemostasis at 3 min
TachoSil (n=59) | 44 | 75% | [0.635; 0.857] | <0.0001
Comparator [Hemostatic fleece material without additional active coagulation stimulating compounds] (n=60) | 20 | 33% | [0.214; 0.453] | <0.0001
Hemostasis at 6 min
TachoSil (n=59) | 56 | 95% | [0.893;1.000] | 0.0006
Comparator (n=60) | 43 | 72% | [0.603; 0.831] | 0.0006

14.2 Hepatic

A randomized, open-label, parallel group, multi-center trial comparing TachoSil with comparator was conducted to evaluate TachoSil for the secondary treatment of local bleeding in patients undergoing hepatic surgery.

A total of 114 patients were randomized to treatment with TachoSil and 110 patients were randomized to treatment with comparator. A similar proportion of male patients and female patients were randomly assigned in the trial (53% and 47%, respectively). The mean (SD) age of patients was 58.1 (13.95) years and in both treatment groups approximately 30% of the patients were above 65 years. The majority of patients were White/Caucasian (80%) and the most common ethnicity was non-Hispanic/non-Latino (88%).

A larger proportion of patients in the TachoSil treatment group (81%) than in the comparator treatment group (50%) achieved hemostasis within the first three minutes after treatment application. The primary analysis of the proportion of patients who achieved hemostasis within three minutes showed a statistically significant difference between treatment groups in favor of TachoSil (p<0.001) and obtained a clinical relevant difference between the two groups defined from the estimated odds ratio (see Table 8).

With respect to one of the two secondary endpoints, 108 (95%) patients in the TachoSil group and 84 (76%) patients in the comparator group achieved hemostasis within five minutes in which the secondary analysis also showed a statistically significant difference between the group in favor of TachoSil (p<0.001, multiplicity adjusted) (see Table 8).

Table 8. Efficacy Results in Hepatic Surgery, by Treatment, Intent-To-Treat Population
Treatment | Total number of patients who achieved hemostasis | Percentage of patients who achieved hemostasis | Odds ratio [95% CI] | p-value [Hochberg's adjustment for multiplicity]
Hemostasis at 3 min
TachoSil (n=114) | 92 | 81% | 4.87 [2.55; 9.29] | <0.001
Comparator [Hemostatic fleece material made of oxidized cellulose polymer] (n=110) | 55 | 50% | 4.87 [2.55; 9.29] | <0.001
Hemostasis at 5 min
TachoSil (n=114) | 108 | 95% | 6.24 [2.39;16.30] | <0.001
Comparator (n=110) | 84 | 76% | 6.24 [2.39;16.30] | <0.001
Time to hemostasis [Analyzed by a log rank test for equality over treatments. Patients who did not achieve hemostasis after 10 minutes were censored in the analysis.] | - | - | - | <0.001
TachoSil (n=114) | - | - | - | <0.001
Comparator (n=110) | - | - | - | <0.001

14.3 Pediatric

In a pediatric subset of a randomized, open-label, parallel group, multi-center trial comparing TachoSil with comparator the efficacy of TachoSil for the secondary treatment of local bleeding in pediatric patients undergoing hepatic surgery was evaluated.

In the randomized part of the study, eight patients were treated with TachoSil and nine patients were treated with the comparator. After the randomization phase, an additional 12 patients were treated with TachoSil in a single extension arm to reach 20 patients exposed to TachoSil. A similar proportion of male and female pediatric patients were treated overall in the trial (48% and 52%, respectively). The majority of patients were White/Caucasian (79%) and the most common ethnicity was non-Hispanic/non-Latino (69%). The mean age was slightly higher in the TachoSil group (4.58 years; range 0.4, 13.0 years) than in the comparator group (3.77 years; range 0.4, 16.0 years).

A larger proportion of the patients in the TachoSil group (7/8 [88%]) than in the comparator group (4/9 [44%]) achieved hemostasis within three minutes in the randomized part of the study. The results were similar considering the whole set of pediatric patients exposed to TachoSil (17/20 [85%]) (see Table 9). No statistical testing was performed of the difference between the two groups due to the small sample size. Seven patients in the TachoSil group (88%) and seven patients in the comparator group (78%) achieved hemostasis within five minutes (see Table 9).

Table 9. Achievement of Hemostasis of Pediatric Patients Undergoing Hepatic Surgery, Intent-To-Treat Population/Safety Population
Treatment | Total number of achieved hemostasis | Percentage of patients | Exact [95% CI]
Hemostasis at 3 min
TachoSil (n=8) | 7 | 88% | [47.3, 99.7]
Comparator [Hemostatic fleece material made of oxidized cellulose polymer] (n=9) | 4 | 44% | [13.7, 78.8]
Hemostasis at 5 min
TachoSil (n=8) | 7 | 88% | [47.3, 99.7]
Comparator (n=9) | 7 | 78% | [40.0, 97.2]
All TachoSil Patients [Safety analysis set]
Hemostasis at 3 min | 17 | 85% | [62.1, 96.8]
TachoSil (n=20) | 17 | 85% | [62.1, 96.8]
Hemostasis at 5 min | 19 | 95% | [75.1, 99.9]
TachoSil (n=20) | 19 | 95% | [75.1, 99.9]

In another clinical study, 16 pediatric patients were included in a prospective, multi-center, uncontrolled, study where TachoSil was used in connection with resection of the liver with or without segmental liver transplantation.

The analysis of the efficacy parameter, time to hemostasis, showed that 13 of 16 patients achieved hemostasis within three minutes after application of TachoSil. One patient obtained hemostasis eight minutes after treatment application and two subjects failed to achieve satisfactory hemostasis within 10 minutes, which necessitated alternative hemostatic measures.

The estimated proportion of patients achieving hemostasis within three minutes was 81%, which is considered similar to results seen in the randomized controlled study.

16 HOW SUPPLIED/STORAGE AND HANDLING

Each TachoSil patch is packaged individually in a tray with lidding. This is placed in an outer pouch with a desiccant bag and packaged into a folding carton.

TachoSil is supplied in the following pack sizes:

- Package with 1 patch of 3.7 inch x 1.9 inch (9.5 cm x 4.8 cm) | (NDC 83078-701-01)
- Package with 2 patches of 1.9 inch x 1.9 inch (4.8 cm x 4.8 cm) | (NDC 83078-702-02)

Storage

- Use TachoSil before expiration date indicated on the package.
- Store unopened packages of TachoSil between 2ºC and 25ºC. TachoSil does not require refrigeration. Do not freeze.
- Do not use if package is opened or damaged.

17 PATIENT COUNSELING INFORMATION

- Because TachoSil may cause the formation of clots in blood vessels if exposed intravascularly, advise patients to consult their physician if they experience chest pain, shortness of breath or difficulty speaking or swallowing, or leg tenderness or swelling [see Warnings and Precautions (5.1)].
- Instruct patients to consult their physician if symptoms of B19 virus infection appear (fever, drowsiness and chills) followed about two weeks later by a rash and joint pain. Parvovirus B19 most seriously affects pregnant women (fetal infection); immune-compromised individuals or individuals with an increased erythropoiesis (e.g., hemolytic anemia) [see Warnings and Precautions (5.7)].
- Advise patients that, because TachoSil is made from human blood, it may carry a risk of transmitting infectious agents (e.g., viruses), and theoretically, the Creutzfeldt-Jakob (CJD) agent [see Warnings and Precautions (5.7)].

Manufactured by:

Corza Medical Distribution GmbH, Austria Branch
St. Peter Strasse 25
A-4020 Linz
Austria

Distributed by:
Corza Medical GmbH
Speditionstrasse 21
40221 Duesseldorf, Germany

U.S. License No. 2294

TachoSil is a registered trademark licensed to Corza Medical GmbH

All other trademarks are the property of their respective owners.

PRINCIPAL DISPLAY PANEL - 1 Patch Blister Pack Pouch Carton - NDC 83078-701-01

NDC 83078-701-01

Fibrin
Sealant Patch
TachoSil®

3.7 inch x 1.9 inch
(9.5 cm x 4.8 cm)

Contents: 1 absorbable fibrin sealant patch

Single use only

Topical use only
Do not use intravascularly

Store at 2°C to 25°C (36°F to 77°F)
Do not freeze

Directions for use: See package insert

Do not use if package is opened or damaged

Use immediately once the foil pouch is opened
Do not resterilize

Dispose of any unused product or waste material
in accordance with local requirements

Rx Only

Product Code 1144922

Corza

PRINCIPAL DISPLAY PANEL - 1 Patch Blister Pack Sample Pouch Carton - NDC 83078-704-01

NDC 83078-704-01

Fibrin
Sealant Patch
TachoSil®

Sample - Not for Sale

3.7 inch x 1.9 inch
(9.5 cm x 4.8 cm)

Contents: 1 absorbable fibrin sealant patch

Single use only

Topical use only
Do not use intravascularly

Store at 2°C to 25°C (36°F to 77°F)
Do not freeze

Directions for use: See package insert

Do not use if package is opened or damaged

Use immediately once the foil pouch is opened
Do not resterilize

Dispose of any unused product or waste material
in accordance with local requirements

Rx Only

Product Code 6019646

Corza

PRINCIPAL DISPLAY PANEL - 2 Patch Blister Pack Pouch Carton NDC 83078-702-02

NDC 83078-702-02

Fibrin
Sealant Patch
TachoSil®

1.9 inch x 1.9 inch
(4.8 cm x 4.8 cm)

Contents: 2 absorbable fibrin sealant patches

Single use only

Topical use only
Do not use intravascularly

Store at 2°C to 25°C (36°F to 77°F)
Do not freeze

Directions for use: See package insert

Do not use if package is opened or damaged

Use immediately once the foil pouch is opened
Do not resterilize

Dispose of any unused product or waste material
in accordance with local requirements

Rx Only

Product Code 1144923

Corza